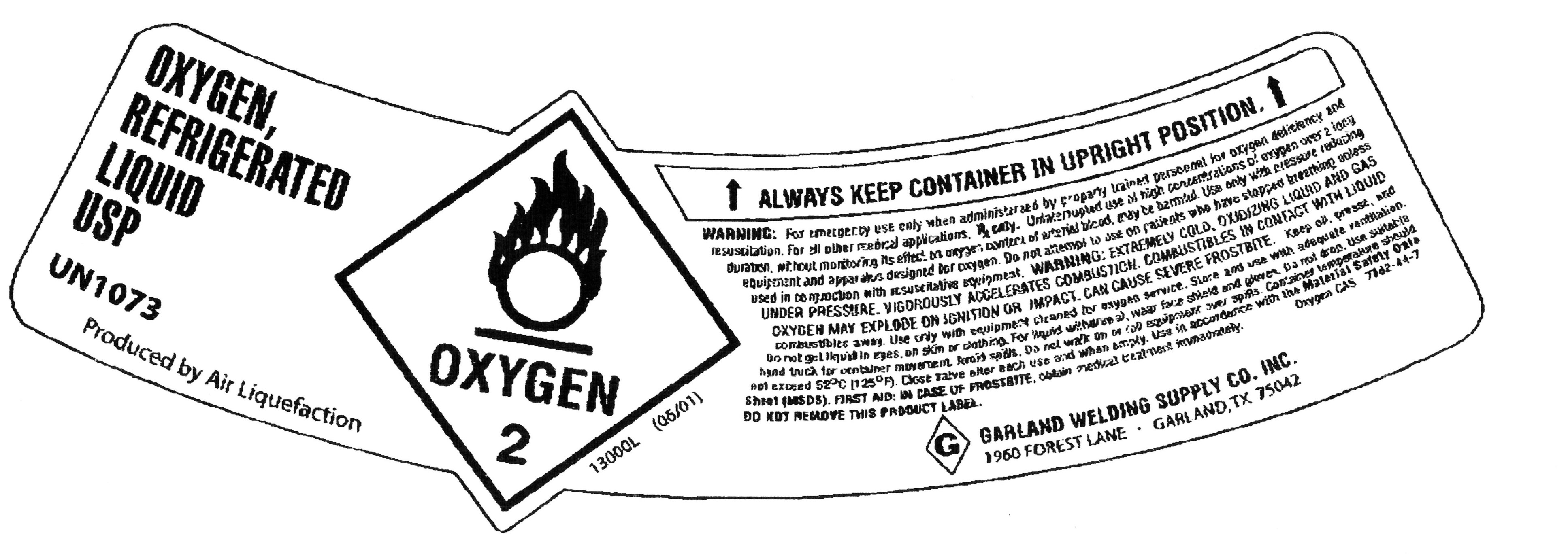 DRUG LABEL: Oxygen
NDC: 66414-001 | Form: GAS
Manufacturer: Garland Welding Supply Company
Category: prescription | Type: HUMAN PRESCRIPTION DRUG LABEL
Date: 20100329

ACTIVE INGREDIENTS: Oxygen 992 mL/1 L

oxygen

PACKAGE LABEL

OXYGEN, REFRIGERATED LIQUID USP UN1073
PRODUCED BY AIR LIQUEFACTION
OXYGEN 2
13000L (05/01)
ALWAYS KEEP CONTAINER IN UPRIGHT POSITION.
WARNING: For emergency use only when administered by properly trained personnel for oxygen deficiency and resuscitation. For all other medical applications, Rx only. Uninterrupted use of high concentrations of oxygen over a long period of time without monitoring its effect on oxygen content of arterial blood may be harmful. Use with only pressure reducing equipment and apparatus designed for oxygen. Do not attempt to use on patients who have stopped breathing unless used in conjunction with resuscitative equipment. WARNING: EXTREMELY COLD, OXIDIZING LIQUID AND GAS. OXYGEN MAY EXPLODE ON IGNITION OR IMPACT. CAN CAUSE SEVERE FROSTBITE. Keep oil, grease, and combustibles away. Use only with equipment cleaned for oxygen service. Store and use with adequate ventilation. Do not get liquid in eyes, on skin or clothing. For liquid withdrawal, wear face shield and gloves. Do not drop. Use suitable hand truck for container movement. Avoid spills. Do not walk on or roll equipment over spills. Container temperature should not exceed 52C (125F). Close valve after each use and when empty. Use in accordance with the Material Safety Data Sheet (MSDS). FIRST AID: IN CASE OF FROSTBITE, obtain medical treatment immediately. Oxygen CAS: 7782-44-7. DO NOT REMOVE THIS PRODUCT LABEL.
GARLAND WELDING SUPPLY, INC. 1960 FOREST LANE GARLAND, TX 75042